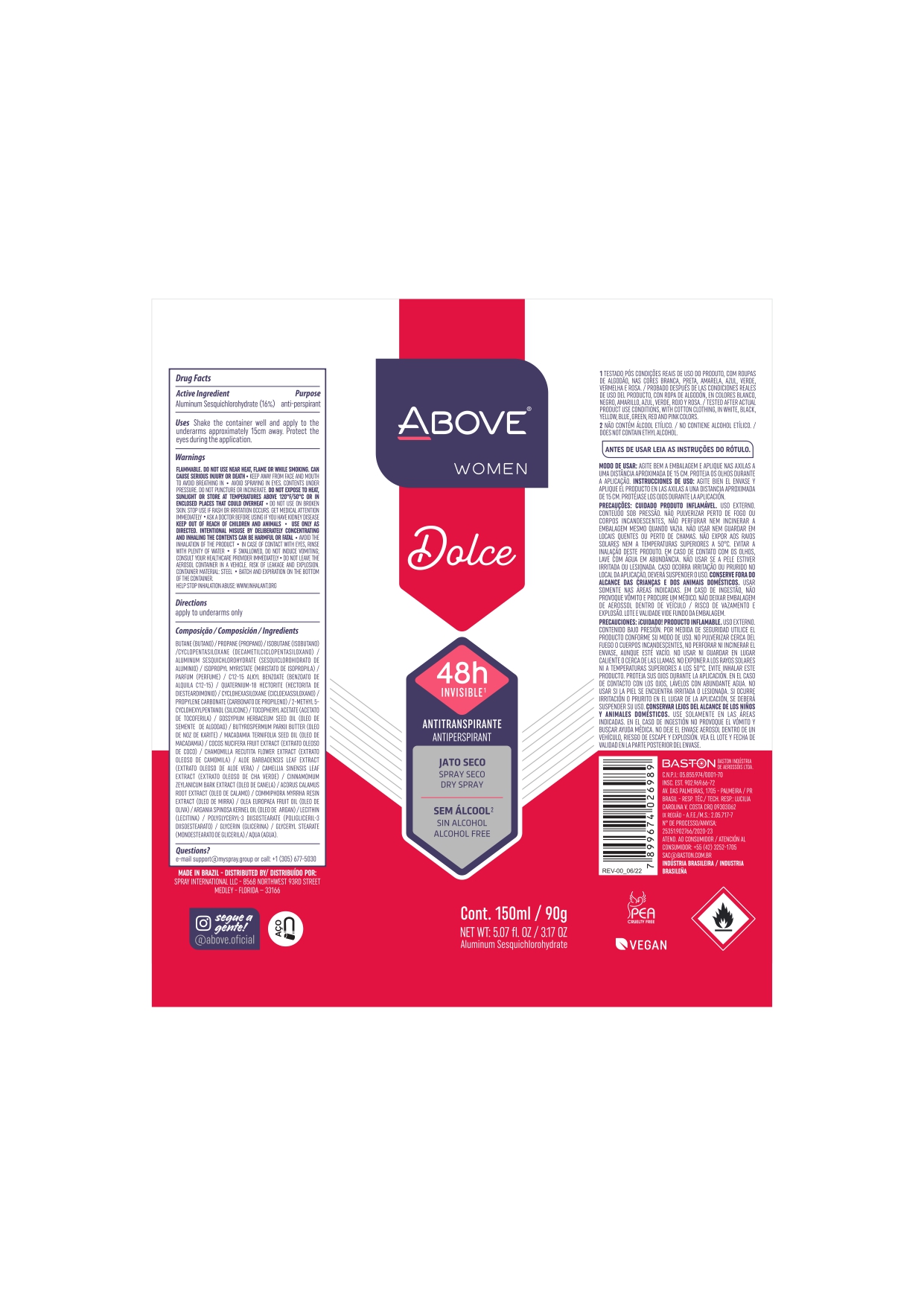 DRUG LABEL: ANTIPERSPIRANT ABOVE WOMEN DOLCE
NDC: 73306-1127 | Form: AEROSOL
Manufacturer: Baston Indústria de Aerossóis LTDA
Category: otc | Type: HUMAN OTC DRUG LABEL
Date: 20240503

ACTIVE INGREDIENTS: ALUMINUM SESQUICHLOROHYDRATE 24 g/100 g
INACTIVE INGREDIENTS: GLYCERIN; POLYGLYCERYL-3 DIISOSTEARATE; ACORUS CALAMUS ROOT; BUTANE; PROPANE; LEVANT COTTON SEED; COCONUT; ALLANTOIN; GREEN TEA LEAF; DIMETHICONE; ARGAN OIL; WATER; CINNAMON BARK OIL; MACADAMIA OIL; ALPHA-TOCOPHEROL ACETATE; VINYL DIMETHICONE/METHICONE SILSESQUIOXANE CROSSPOLYMER; MYRRH OIL; SHEA BUTTER; ALOE VERA LEAF; SILICA DIMETHYL SILYLATE; LECITHIN, SOYBEAN; GLYCERYL MONOSTEARATE; CHAMOMILE; ISOBUTANE; DISTEARDIMONIUM HECTORITE; ISOPROPYL MYRISTATE; AVOCADO OIL; CYCLOMETHICONE 5; PROPYLENE CARBONATE

ABOVE WOMEN DOLCE

Aluminum Sesquichlorohydrate 16%

Aluminum Sesquichlorohydrate 24%

PURPOSE

Antiperspirant

INDICATIONS AND USAGE

Uses - reduces underarm wetness

DOSAGE AND ADMINISTRATION

Directions - apply to underaerms only

INACTIVE INGREDIENT

BUTANE/PROPANE/ISOBUTANE/CYCLOPENTASILOXANE/DIMETHICONE/ISOPROPYL MYRISTATE/C12-15 ALKYL BENZOATE/
QUATERNIUM-18 HECTORITE/PROPYLENE CARBONATE/CYCLOHEXASILOXANE/SILICA/TOCOPHERYL ACETATE/GOSSYPIUM HERBACEUM SEED OIL/
DIMETHICONE/VINYL DIMETHICONE CROSSPOLYMER/GLYCINE SOJA OIL/ALLANTOIN/BUTYROSPERMUM PARKII BUTTER/MACADAMIA TERNIFOLIA SEED OIL/
COCOS NUCIFERA FRUIT EXTRACT/CHAMOMILLA RECUTITA FLOWER EXTRACT/ALOE BARBADENSIS LEAF EXTRACT/CAMELLIA SINENSIS LEAF EXTRACT/
CINNAMOMUM ZEYLANICUM BARK EXTRACT/ACORUS CALAMUS ROOT EXTRACT/COMMIPHORA MYRRHA RESIN EXTRACT/OLEA EUROPAEA FRUIT OIL/
PERSEA GRATISSIMA OIL/ARGANIA SPINOSA KERNEL OIL/LECITHIN/POLYGLYCERYL-3 DIISOSTEARATE/GLYCERIN/GLYCERYL STEARATE/CYCLOTETRASILOXANE/
AQUA/PARFUM(BUTYLPHENYL METHYLPROPIONAL/COUMARIN/HEXYL CINNAMAL/HYDROXYCITRONELLAL/LIMONENE).

QUESTIONS

e-mail sac@baston.com.br or call: +1(305)677-5030

WARNINGS

Flammable until fully dry. Do not use near heat, Flame or while smoking. Can cause serious injury or deat. Keep away from face and mouth to avoid breathing in. Avoid spraying in eyes. Contents under preassure. Do not puncture ou incinerate. Do not expose to heat or store at temperatures above 120 °F/ 50°C ou in enclosed places that could overheat. Do not use on broken skin. Stop use if rash or irritation accours. Get medical attention immediately. Ask a doctor before using if you have kidney disease. Keep out of reac of children and animals. Use only as direct. Intentional misuse by deliberately concentrating and inhaling the contents can be harmful or fatal. Avoid the inhalation of the product. In case of contact with eyes, rinse whit planty of water. Is swallowed , do not induce vomiting. Consulte your healthcare provider immediatly. Do not leave the aerosol container in a vehicle, risk of leakage and explosion. Container material: STEEL. Batch and expiration on bottom of the container. Help stop the inhalation abuse: www.inhalant.org

Keep Out Of Reach Of Children